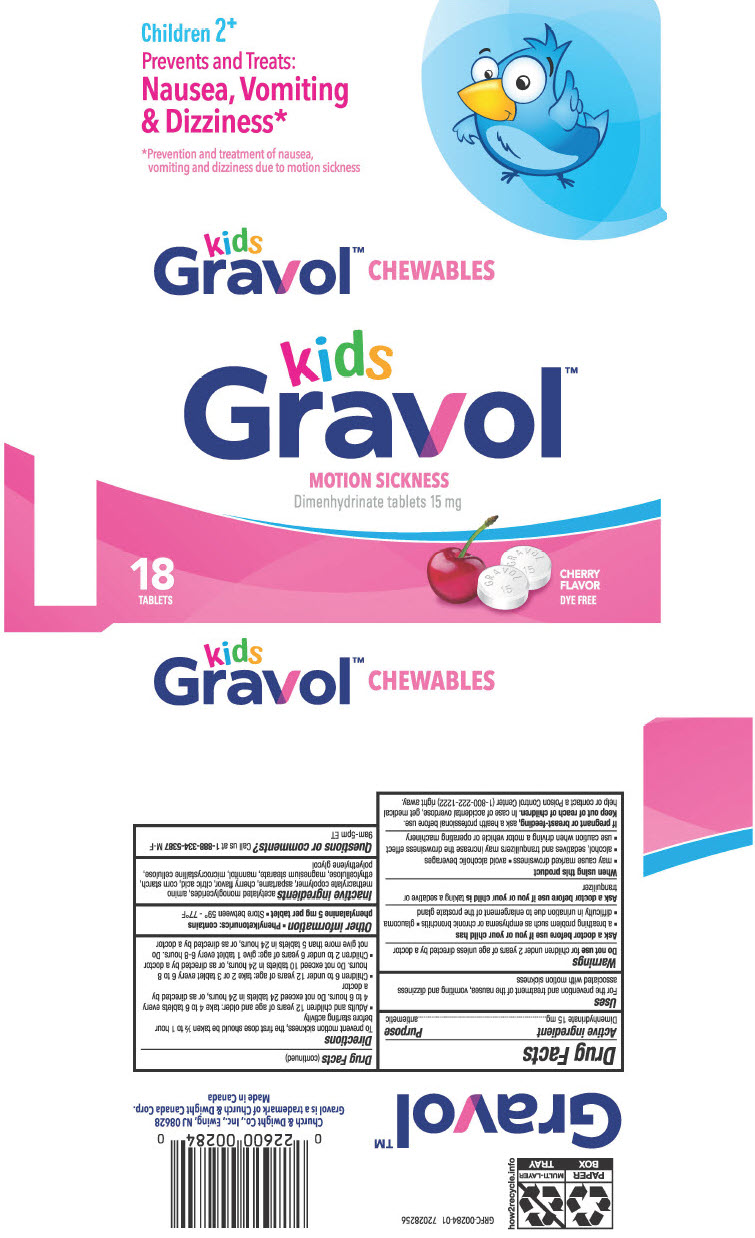 DRUG LABEL: Kids Gravol Chewables Motion Sickness Dimenhydrinate
NDC: 10237-944 | Form: TABLET, CHEWABLE
Manufacturer: Church & Dwight Co., Inc.
Category: otc | Type: HUMAN OTC DRUG LABEL
Date: 20240301

ACTIVE INGREDIENTS: DIMENHYDRINATE 15 mg/1 1
INACTIVE INGREDIENTS: DIACETYLATED MONOGLYCERIDES; DIMETHYLAMINOETHYL METHACRYLATE - BUTYL METHACRYLATE - METHYL METHACRYLATE COPOLYMER; ASPARTAME; CITRIC ACID MONOHYDRATE; STARCH, CORN; ETHYLCELLULOSE, UNSPECIFIED; MAGNESIUM STEARATE; MANNITOL; MICROCRYSTALLINE CELLULOSE; POLYETHYLENE GLYCOL, UNSPECIFIED

Kids Gravol™ Chewables Motion Sickness Dimenhydrinate

Drug Facts

Active ingredient

Dimenhydrinate 15 mg

Purpose

antiemetic

Uses

For the prevention and treatment of the nausea, vomiting and dizziness associated with motion sickness

Warnings

Do not use for children under 2 years of age unless directed by a doctor

Ask a doctor before use if you or your child has

- a breathing problem such as emphysema or chronic bronchitis
- glaucoma
- difficulty in urination due to enlargement of the prostate gland

Ask a doctor before use if you or your child is taking a sedative or tranquilizer

When using this product

- may cause marked drowsiness
- avoid alcoholic beverages
- alcohol, sedatives and tranquilizers may increase the drowsiness effect
- use caution when driving a motor vehicle or operating machinery

PREGNANCY OR BREAST FEEDING

If pregnant or breast-feeding, ask a health professional before use.

Keep out of reach of children. In case of accidental overdose, get medical help or contact a Poison Control Center (1-800-222-1222) right away.

Directions

To prevent motion sickness, the first dose should be taken ½ to 1 hour before starting activity

- Adults and children 12 years of age and older: take 4 to 6 tablets every 4 to 6 hours. Do not exceed 24 tablets in 24 hours, or as directed by a doctor
- Children 6 to under 12 years of age: take 2 or 3 tablet every 6 to 8 hours. Do not exceed 10 tablets in 24 hours, or as directed by a doctor
- Children 2 to under 6 years of age: give 1 tablet every 6-8 hours. Do not give more than 5 tablets in 24 hours, or as directed by a doctor

Other information

- Phenylketonurics: contains phenylalanine 5 mg per tablet
- Store between 59° - 77°F

Inactive ingredients

acetylated monoglycerides, amino methacrylate copolymer, aspartame, cherry flavor, citric acid, corn starch, ethylcellulose, magnesium stearate, mannitol, microcrystalline cellulose, polyethylene glycol

Questions or comments?

Call us at 1-888-334-5387 M-F 9am-5pm ET

PRINCIPAL DISPLAY PANEL - 15 mg Blister Pack Carton

kids
Gravol™
MOTION SICKNESS
Dimenhydrinate tablets 15 mg

18
TABLETS

CHERRY
FLAVOR

DYE FREE